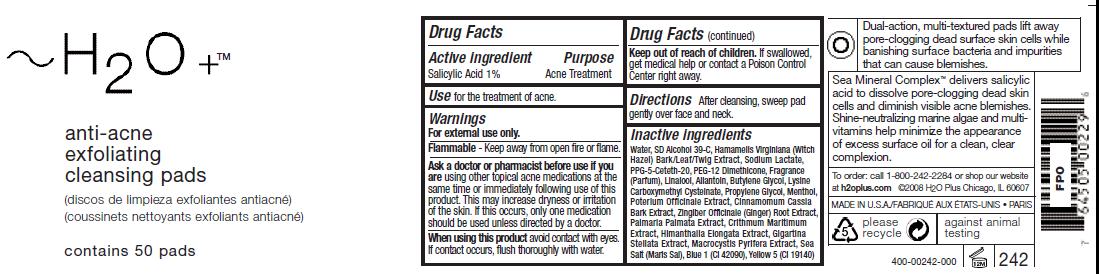 DRUG LABEL: Anti Acne Exfoliating Cleansing Pads
NDC: 65903-242 | Form: SWAB
Manufacturer: H2O Plus
Category: otc | Type: HUMAN OTC DRUG LABEL
Date: 20110928

ACTIVE INGREDIENTS: Salicylic Acid 10 uL/1 mL
INACTIVE INGREDIENTS: Water; ALCOHOL; HAMAMELIS VIRGINIANA BARK; SODIUM LACTATE; PPG-5-CETETH-20; PEG-12 DIMETHICONE; LINALOOL, (+/-)-; BUTYLENE GLYCOL; CARBOCYSTEINE LYSINE; PROPYLENE GLYCOL; MENTHOL; SANGUISORBA MINOR ROOT; CHINESE CINNAMON; GINGER; DULSE; CRITHMUM MARITIMUM; HIMANTHALIA ELONGATA; MASTOCARPUS STELLATUS; MACROCYSTIS PYRIFERA; SEA SALT

Drug Facts

Active ingredient
Salicylic Acid 1%

Purpose
Acne Treatment

Warnings
For external use only.
Flammable - Keep away from open fire or flame.

Ask a doctor or pharmacist before use if you
are using other topical acne medications at the
same time or immediately following use of this
product. This may increase dryness or irritation
of the skin. If this occurs, only one medication
should be used unless directed by a doctor.

INDICATIONS AND USAGE

Use for the treatment of acne.

Keep out of reach of children. If swallowed,
get medical help or contact a Poison Control
Center right away.

DOSAGE AND ADMINISTRATION

Directions After cleansing, sweep pad
gently over face and neck.

Inactive ingredients
Water, SD Alcohol 39-C, Hamamelis Virginiana (Witch
Hazel) Bark/Leaf/Twig Extract, Sodium Lactate,
PPG-5-Ceteth-20, PEG-12 Dimethicone, Fragrance
(Parfum), Linalool, Allantoin, Butylene Glycol, Lysine
Carboxymethyl Cysteinate, Propylene Glycol, Menthol,
Poterium Officinale Extract, Cinnamomum Cassia
Bark Extract, Zingiber Officinale (Ginger) Root Extract,
Palmaria Palmata Extract, Crithmum Maritimum
Extract, Himanthalia Elongata Extract, Gigartina
Stellata Extract, Macrocystis Pyrifera Extract, Sea
Salt (Maris Sal), Blue 1 (CI 42090), Yellow 5 (CI 19140)

Image of label aaep242.jpg